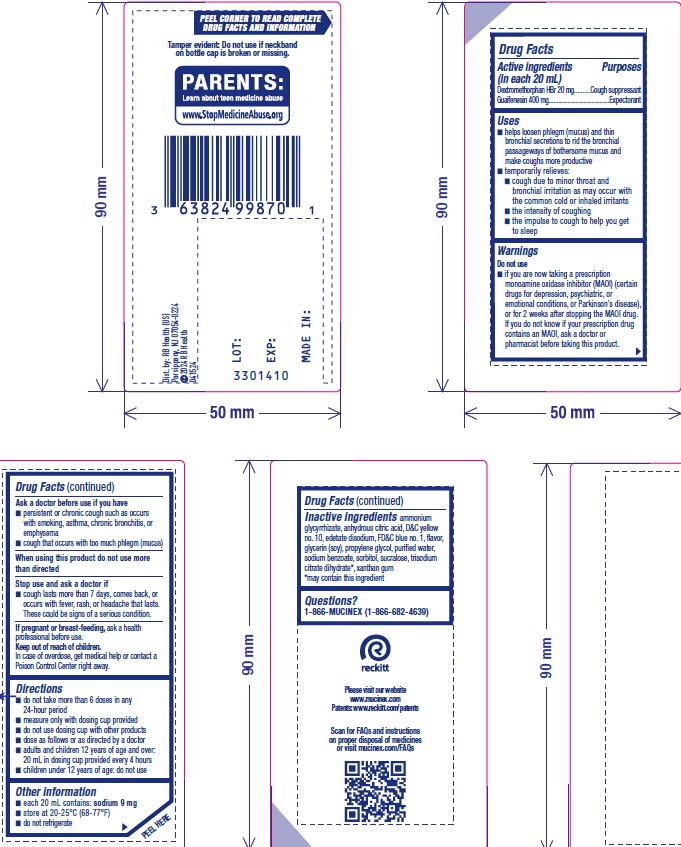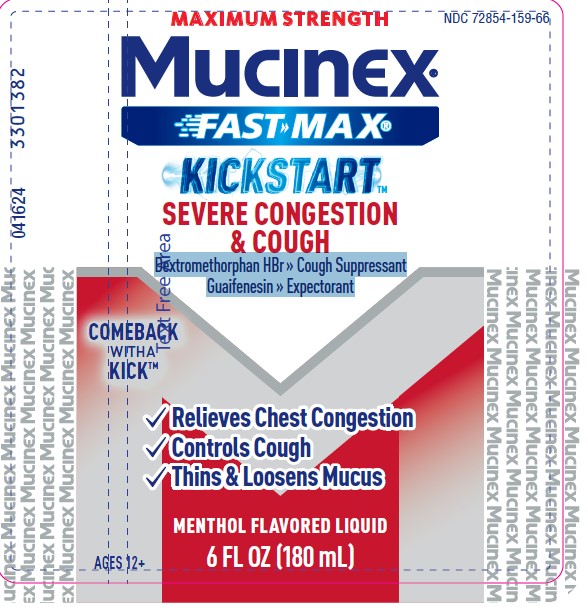 DRUG LABEL: Mucinex Fast-Max Kickstart Severe Congestion and Cough
NDC: 72854-159 | Form: LIQUID
Manufacturer: RB Health (US) LLC
Category: otc | Type: HUMAN OTC DRUG LABEL
Date: 20240522

ACTIVE INGREDIENTS: GUAIFENESIN 400 mg/1 1; DEXTROMETHORPHAN HYDROBROMIDE 20 mg/1 1
INACTIVE INGREDIENTS: SODIUM BENZOATE; SORBITOL; WATER; XANTHAN GUM; D&C YELLOW NO. 10; PROPYLENE GLYCOL; EDETATE DISODIUM; SUCRALOSE; ANHYDROUS CITRIC ACID; AMMONIUM GLYCYRRHIZATE; FD&C BLUE NO. 1; TRISODIUM CITRATE DIHYDRATE; GLYCERIN

Mucinex Fast-Max Kickstart Severe Congestion & Cough

Active ingredients
(in each 20 mL)
Dextromethorphan HBr 20 mg
Guaifenesin 400 mg

Uses

■ helps loosen phlegm (mucus) and thin
bronchial secretions to rid the bronchial
passageways of bothersome mucus and
make coughs more productive
■ temporarily relieves:
■ cough due to minor throat and
bronchial irritation as may occur with
the common cold or inhaled irritants
■ the intensity of coughing
■ the impulse to cough to help you get
to sleep

Warnings

Do not use
■ if you are now taking a prescription
monoamine oxidase inhibitor (MAOI) (certain
drugs for depression, psychiatric, or
emotional conditions, or Parkinson’s disease),
or for 2 weeks after stopping the MAOI drug.
If you do not know if your prescription drug
contains an MAOI, ask a doctor or
pharmacist before taking this product.

Ask a doctor before use if you have
■ persistent or chronic cough such as occurs
with smoking, asthma, chronic bronchitis, or
emphysema
■ cough that occurs with too much phlegm (mucus)

When using this product do not use more
than directed

Stop use and ask a doctor if
■ cough lasts more than 7 days, comes back, or
occurs with fever, rash, or headache that lasts.
These could be signs of a serious condition.

Directions

■ do not take more than 6 doses in any
24-hour period
■ measure only with dosing cup provided
■ do not use dosing cup with other products
■ dose as follows or as directed by a doctor
■ adults and children 12 years of age and over:
20 mL in dosing cup provided every 4 hours
■ children under 12 years of age: do not use

Other information
■ each 20 mL contains: sodium 9 mg
■ store at 20-25°C (68-77°F)
■ do not refrigerate

KEEP OUT OF REACH OF CHILDREN

If pregnant or breast-feeding, ask a health
professional before use.

Keep out of reach of children.
In case of overdose, get medical help or contact a
Poison Control Center right away.

Inactive ingredients

ammonium, glycyrrhizate, anhydrous citric acid, D&C yellow
no. 10, edetate disodium, FD&C blue no. 1, flavor,
glycerin (soy), propylene glycol, purified water,
sodium benzoate, sorbitol, sucralose, trisodium
citrate dihydrate*, xanthan gum
*may contain this ingredient

Questions?
1-866-MUCINEX (1-866-682-4639)

PURPOSE

Dextromethorphan HBr » Cough Suppressant
Guaifenesin » Expectorant

PACKAGE LABEL

NDC 72854-159-66

Relieves Chest Congestion
Controls Cough
Thins& Loosens Mucus

6 fl oz (180mL)

MENTHOL FLAVORED LIQUID

Dextromethorphan HBr » Cough Suppressant
Guaifenesin » Expectorant

Ages 12+